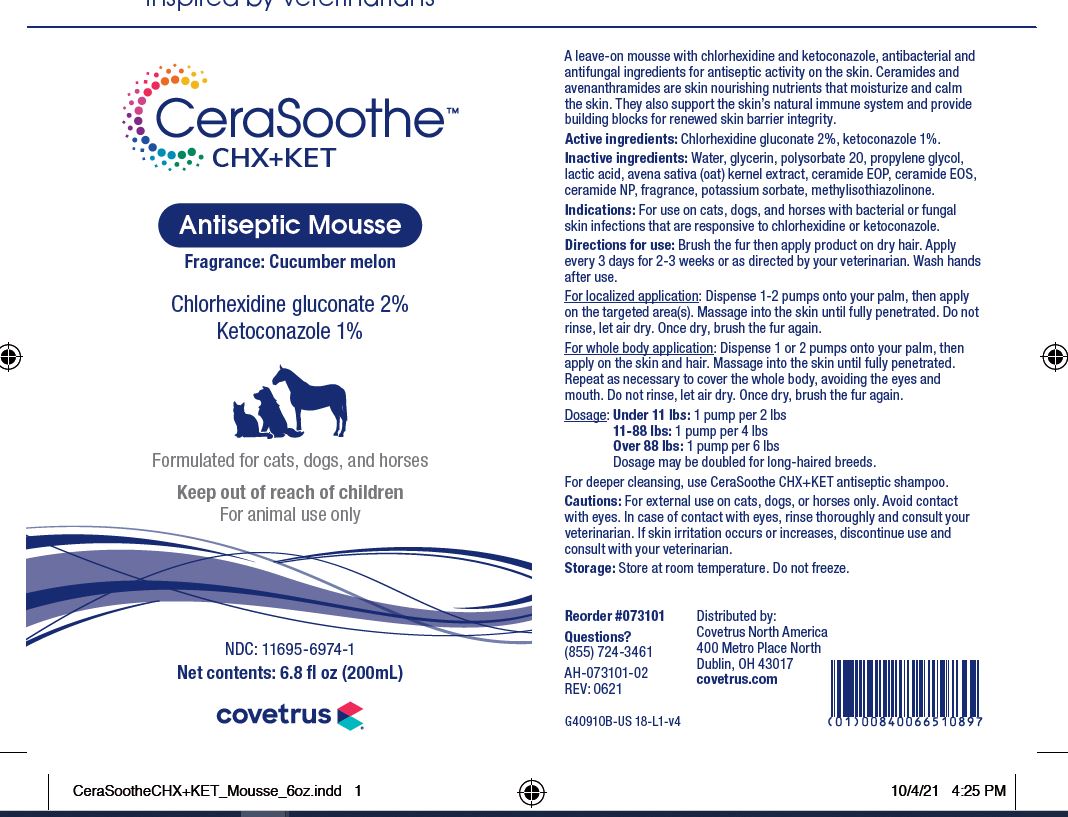 DRUG LABEL: CeraSoothe
NDC: 11695-6974 | Form: LIQUID
Manufacturer: Butler Animal Health Supply, LLC dba Covetrus North America
Category: animal | Type: OTC ANIMAL DRUG LABEL
Date: 20220505

ACTIVE INGREDIENTS: CHLORHEXIDINE GLUCONATE 20 mg/1 mL; KETOCONAZOLE 10 mg/1 mL
INACTIVE INGREDIENTS: WATER; GLYCERIN; POLYSORBATE 20; PROPYLENE GLYCOL; LACTIC ACID; AVENANTHRAMIDES; CERAMIDE 1; CERAMIDE EOS; CERAMIDE NP; POTASSIUM SORBATE; METHYLISOTHIAZOLINONE

DESCRIPTION

CeraSoothe CHX+KET

Antiseptic Mousse

Fragrance: Cucumber melon

A leave-on mousse with chlorhexidine and ketoconazole, antibacterial and antifungal ingredients for antiseptic activity on skin. Ceramides and avenanthramides are skin nourishing nutrients that moisturize and calm the skin. They also support the skin's natural immune system, and provide building blocks for renewed skin barrier integrity.

Active ingredients: Chlorhexidine gluconate 2%, ketoconazole 1%.

Inactive ingredients: Water, glycerin, polysorbate 20, propylene glycol, lactic acid, avena sativa (oat) kernal extract, ceramide EOP, ceramide EOS, ceramide NP, fragrance, potassium sorbate, methylisothiazolinone.

INDICATIONS AND USAGE

Indications: For use on cats, dogs and horses with bacterial or fungal skin infections that are responsive to chlorhexidine or ketoconazole.

Directions for use: Brush the fur and then apply on dry hair. Apply every 3 days for 2 to 3 weeks or as directed by your veterinarian. Wash hands after use.

For localized application: Dispense 1 - 2 pumps onto your palm and then apply on the targeted area(s). Massage into the skin until fully penetrated. Do not rinse, let air dry. Once dry, brush the fur again.

For whole body application: Dispense 1 or 2 pumps onto your palm and then apply on the skin and hair. Massage into the skin until fully penetrated. Repeat as many times and necessary to cover the whole body, avoiding the eyes and mouth. Do not rinse, let air dry. Once dry, brush the fur again.

Dosage:

Under 11 lbs: 1 pump per 2 lbs

11-88 lbs: 1 pump per 4 lbs

Over 88 lbs: 1 pump per 6 lbs

Dosage may be doubled for long-haired breeds. For deeper cleansing, use Ceraven CHX+KET antiseptic shampoo.

WARNINGS AND PRECAUTIONS

Cautions: For external use on cats, dogs and horses only. Avoid contact with eyes. In case of contact with eyes, rinse thoroughly and consult your veterinarian. If skin irritation occurs or increases, discontinue use and consult with your veterinarian.

STORAGE AND HANDLING

Storage: Store at controlled room temperature. Do not freeze.

QUESTIONS?

(855) 724-3461

Distributed by:

Covetrus North America

400 Metro Place North

Dublin, OH 43017

covetrus.com

PRINCIPAL DISPLAY PANEL - 6.8 OUNCE (200 mL) Bottle

Inspired by veterinarians

CeraSoothe CHX+KET

Antiseptic Mousse

Fragrance: Cucumber melon

Chlorhexidine gluconate 2%, Ketoconazole 1%

Formulated for cats, dogs, and horses

Keep out of reach of children

For animal use only

NDC: 11695-6974-1

Net contents: 6.8 fl oz (200 mL)

covetrus